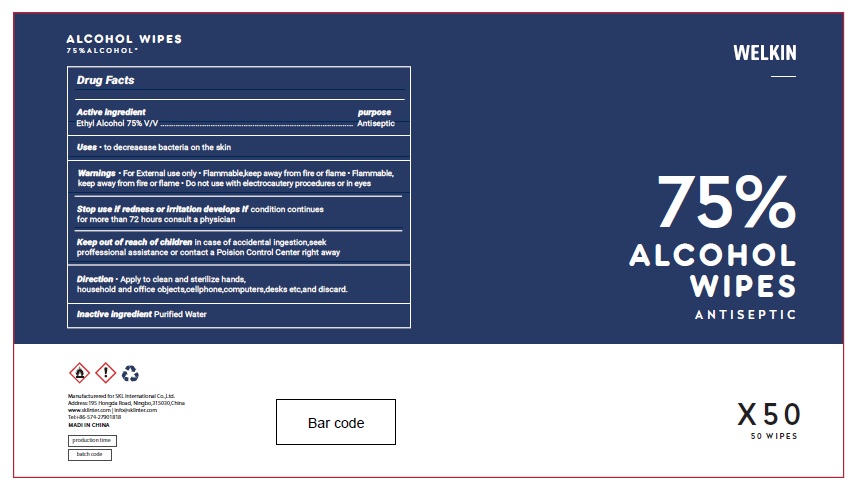 DRUG LABEL: Welkin alcohol wipes
NDC: 74542-013 | Form: CLOTH
Manufacturer: Ningbo SKL International Co.,Ltd.
Category: otc | Type: HUMAN OTC DRUG LABEL
Date: 20200602

ACTIVE INGREDIENTS: ALCOHOL 75 mL/100 mL
INACTIVE INGREDIENTS: WATER

Active Ingredient

Ethyl Alcohol 75% v/v.

Purpose

Antiseptic

Uses

- to decrease bacteria on the skin

Warnings

- For external use only.
- Flammable. Keep away from heat or flame.
- Do not use with electrocautery procedures or in eyes

Stop useif redness or irritation develops. If condition continues for more than 72 hours consult a physician

Keep out of reach of children. If swallowed, get medical help or contact a Poison Control Center right away.

Directions

- Apply to clean and sterilize hands, household and office objects,cellphone,computers,desks etc,and discard.

Inactive ingredients

Purified Water